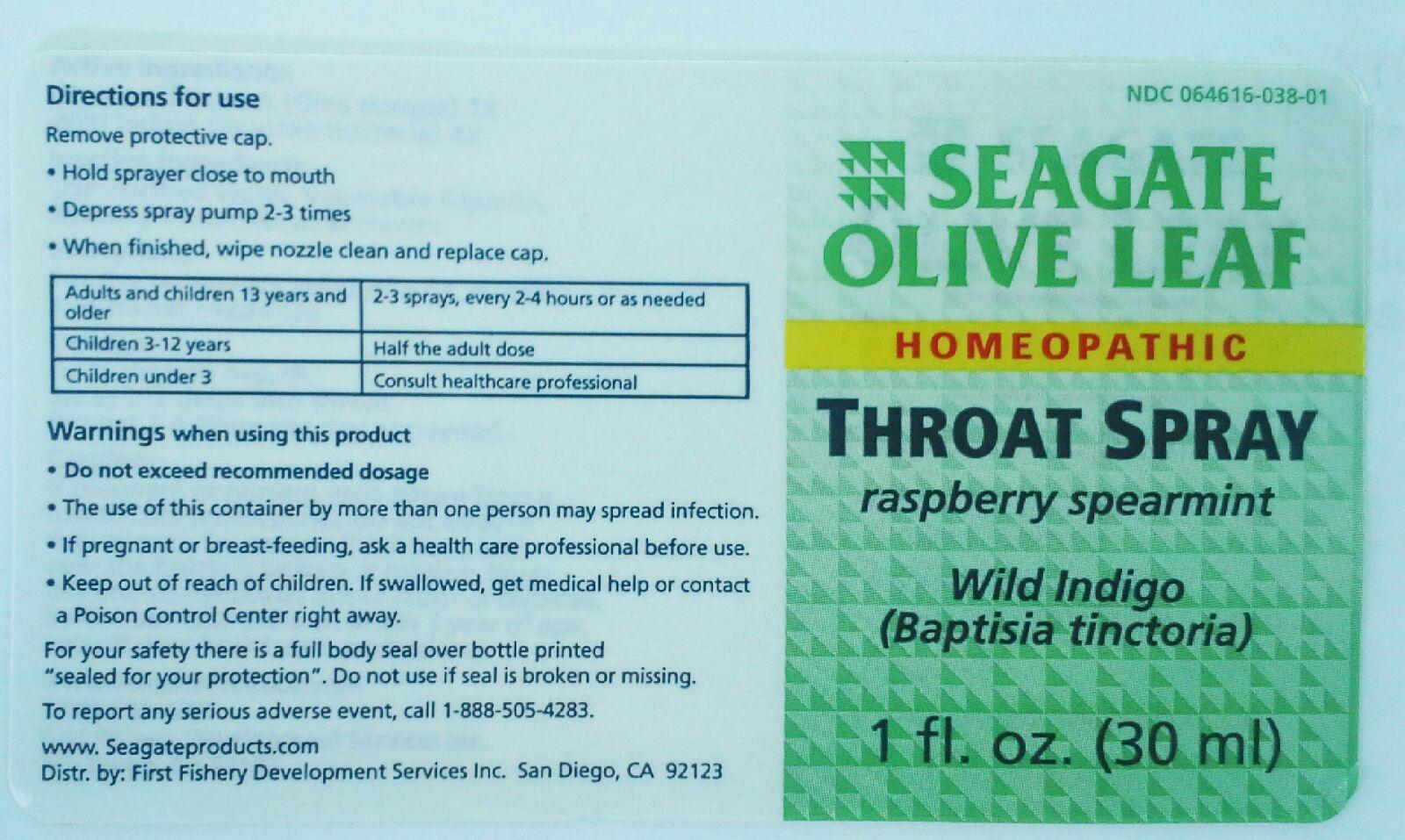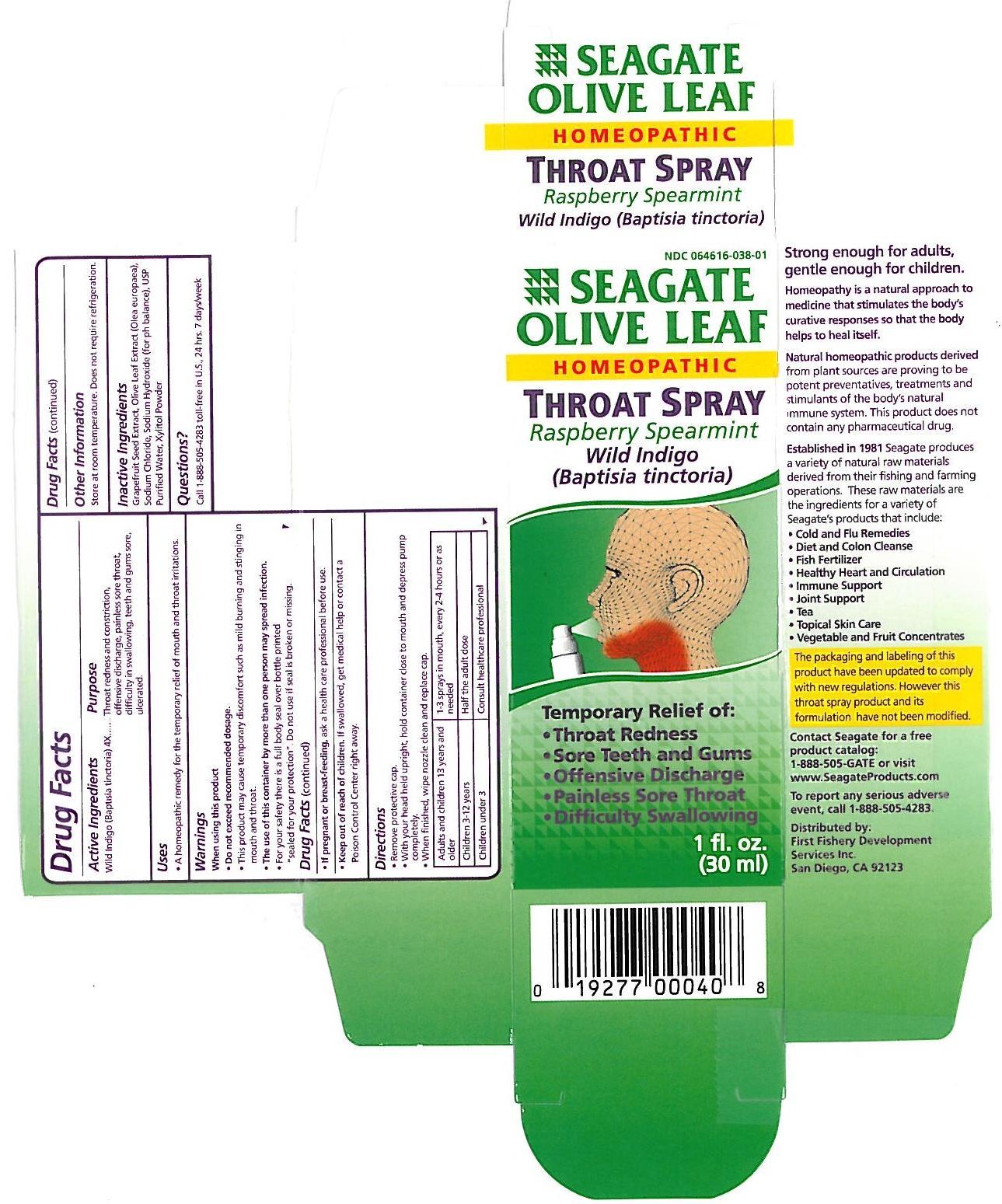 DRUG LABEL: Olive Leaf Throat
NDC: 64616-038 | Form: SPRAY
Manufacturer: Vitality Works, Inc
Category: homeopathic | Type: HUMAN OTC DRUG LABEL
Date: 20251217

ACTIVE INGREDIENTS: BAPTISIA TINCTORIA 4 [hp_X]/1 mL
INACTIVE INGREDIENTS: OLEA EUROPAEA LEAF; XYLITOL; GLYCERIN; WATER; RASPBERRY SEED OIL; SPEARMINT OIL

Olive Leaf Throat Spray Raspberry Spearmint

Olive Leaf Throat Spray Raspberry Spearmint

Wild Indigo (Baptisia tinctoria) 4X

Olive Leaf Throat Spray Raspberry Spearmint

Olive Leaf Extract, Raspberry and Spearmint Natural Flavor, USP Purified Water, Vegetable Glycerin, Xylitol

Olive Leaf Throat Spray Raspberry Spearmint

Keep out of reach of children.

Olive Leaf Throat Spray Raspberry Spearmint

Do not exceed recommended dosage. This product may cause temporary discomfort such as mild burning and stinging in mouth and throat. The use of this container by more than one person may spread infection. For your safety there is a full body seal over bottle printed "sealed for you protection". Do not use if seal is broken or missing.l

Olive Leaf Throat Spray Raspberry Spearmint

A homeopathic remedy for the temporary relief of mouth and throat irritations.

Olive Leaf Throat Spray Raspberry Spearmint

Remove protective cap. With your head held upright, hold container close to mouth and depress pump completely. When finished, wipe nozzle clean and replace cap.

Adults and children 13 years and older - 1-3 sprays in mounth every 2-4 hours or as needed.

Children 3-12 - Half the adult dose.

Children under 3 - Consult healthcare professional.

Olive Leaf Throat Spray Raspberry Spearmint

Throat redness and constriction, offensive discharge, painless sore throat, difficulty in swallowing, teeth and gums sore, ulcerated.